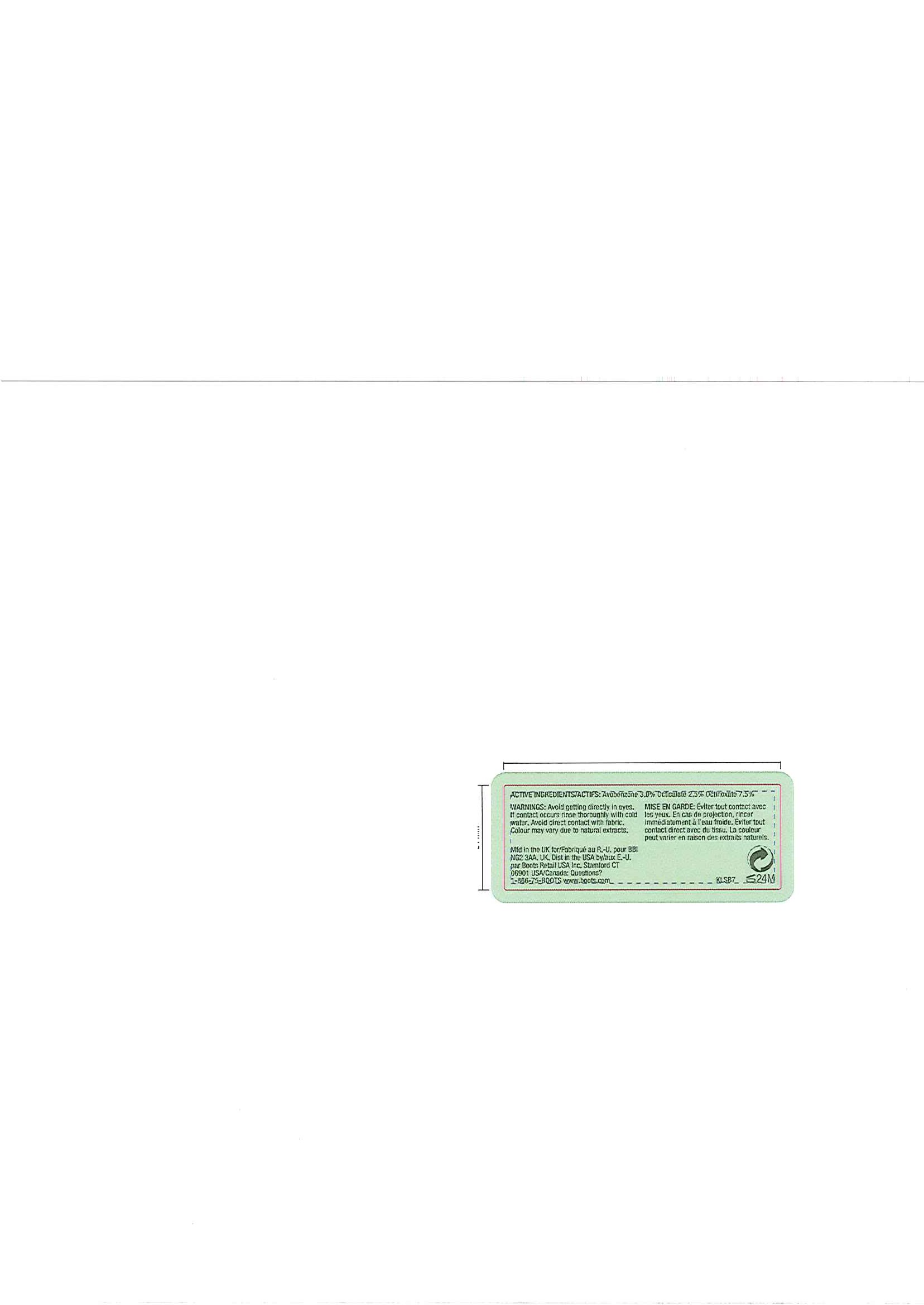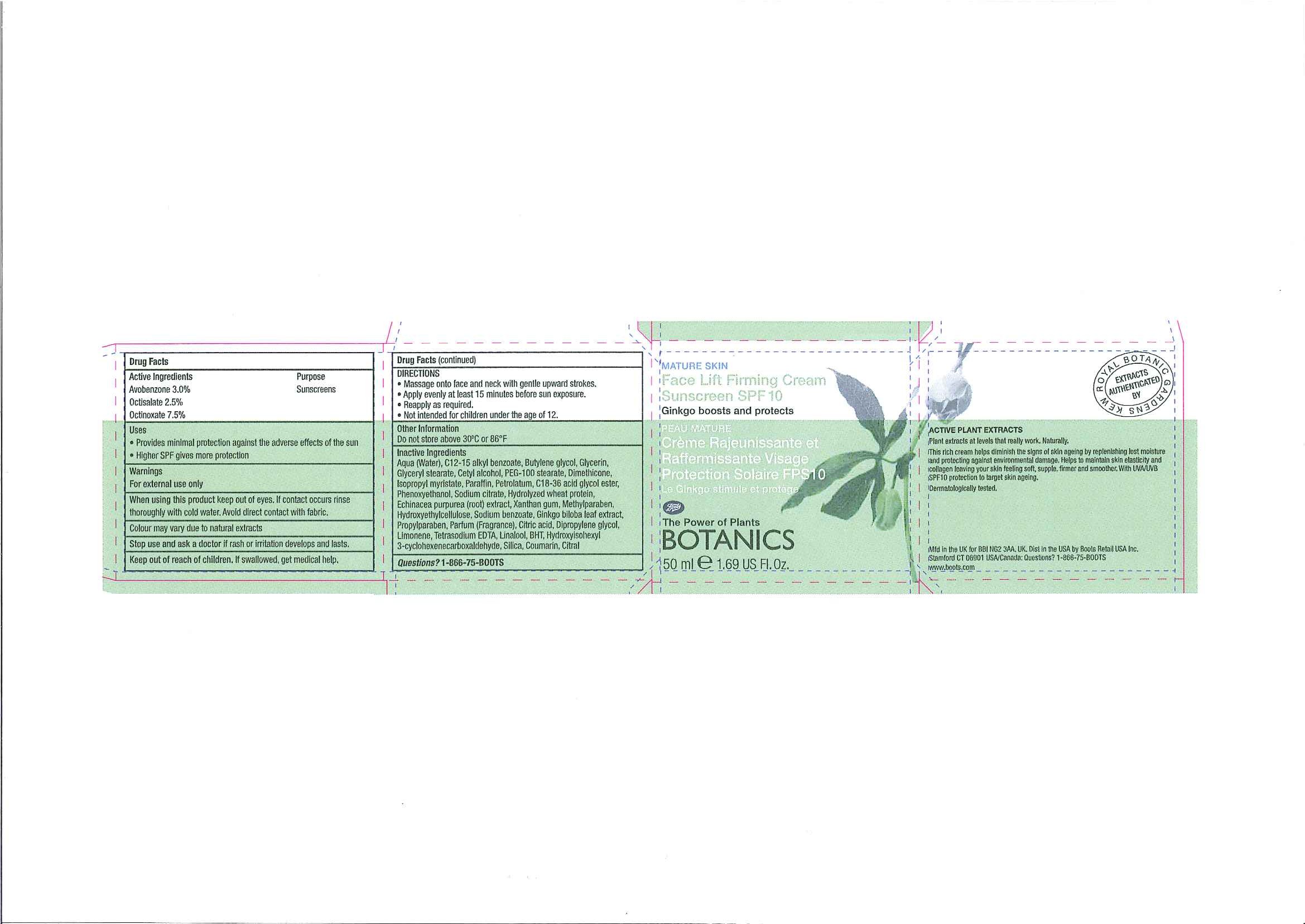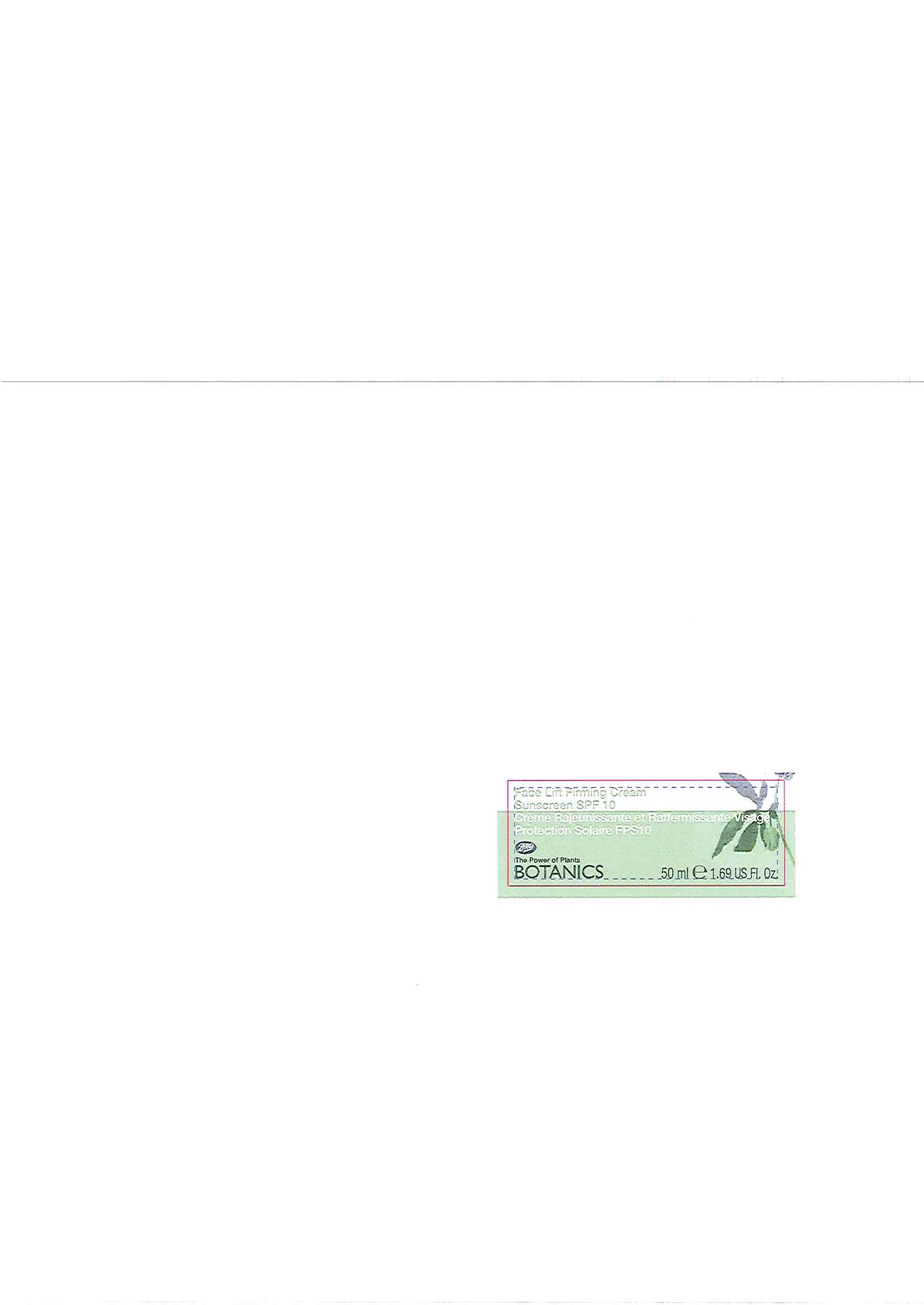 DRUG LABEL: BOTANICS FACE LIFT FIRMING SUNSCREEN SPF 10
NDC: 11489-059 | Form: CREAM
Manufacturer: BCM Ltd
Category: otc | Type: HUMAN OTC DRUG LABEL
Date: 20101207

ACTIVE INGREDIENTS: OCTINOXATE 3.75 mL/50 mL; AVOBENZONE 1.5 mL/50 mL; OCTISALATE 1.25 mL/50 mL
INACTIVE INGREDIENTS: WATER; C12-15 ALKYL BENZOATE; BUTYLENE GLYCOL; GLYCERIN; GLYCERYL MONOSTEARATE; CETYL ALCOHOL; POLYOXYL 100 STEARATE; DIMETHICONE; ISOPROPYL MYRISTATE; PARAFFIN; PETROLATUM; PHENOXYETHANOL; SODIUM CITRATE; WHEAT GLUTEN; ECHINACEA PURPUREA ROOT; XANTHAN GUM; METHYLPARABEN; HYDROXYETHYL CELLULOSE (2000 CPS AT 1%); SODIUM BENZOATE; GINKGO; PROPYLPARABEN; CITRIC ACID MONOHYDRATE; EDETATE SODIUM; BUTYLATED HYDROXYTOLUENE; SILICON DIOXIDE

Carton and Jar labels

ACTIVE INGREDIENT

BOTANICS FACE LIFT FIRMING CREAM SUNSCREEN SPF 10

Drug Facts

Active Ingredients Purpose

Avobenzone 3.0% Sunscreens

Octisalate 2.5%

Octinoxate 7.5%

Uses

- Provides minimal protection against the adverse effects of the sun
- Higher SPF gives more protection

Warnings

For external use only

When using this product keep out of eyes. If contact occurs rinse thoroughly with cold water.

Avoid direct contact with fabric.

HOW SUPPLIED

Colour may vary due to natural extracts

Stop use and ask a doctor if rash or irritation develops and lasts

Keep out of reach of children. If swallowed, get medical help.

Directions

- Massage onto face and neck with gentle upward strokes.
- Apply evenly at least 15 minutes before sun exposure.
- Reapply as required.
- Not intended for children under the age of 12.

Other information

Do not store above 30^0C or 86^0F

Inactive Ingredients

Aqua (Water), C12-15 alkyl benzoate, Butylene glycol, Glycerin, Glyceryl stearate, Cetyl alcohol, PEG-100 stearate, Dimethicone, Isopropyl myristate, Paraffin, Petrolatum, C18-36 acid glycol ester, Phenoxyethanol, Sodium citrate, Hydrolyzed Wheat Protein, Echinacea purpurea (root) extract, Xanthan gum, Methylparaben, Hydroxyethylcellulose, Sodium benzoate, Ginkgo biloba leaf extract, Propylparaben, Parfum (Fragrance), Citric acid, Dipropylene glycol, Limonene, Tetrasodium EDTA, Linalool, BHT, Hydroxyisohexyl 3-cyclohexenecarboxaldehyde, Silica, Coumarin, Citral

Questions? 1-866-75-BOOTS

DESCRIPTION

EXTRACTS AUTHENTICATED BY ROYAL BOTANIC GARDENS KEW

ACTIVE PLANT EXTRACTS

Plant extracts at levels that really work. Naturally.

This rich cream helps diminish the signs of skin ageing by replenishing lost moisture and protecting against environmental damage. Helps to maintain skin elasticity and collagen leaving your skin feeling soft, supple, firmer and smoother. With UVA/UVB SPF10 protection to target skin ageing.

Dermatologically tested.

Carton front label

MATURE SKIN

Face Lift Firming Cream Sunscreen SPF 10

Ginkgo boosts and protects

PEAU MATURE

Crème Rajeunissante et Raffermissante Visage Protection Solaire FPS10

Le Ginkgo stimule et protège

Boots

The Power of Plants

BOTANICS

50ml e 1.69 US Fl. Oz

Face Lift Firming Cream carton.jpg

PACKAGE LABEL

Face Lift Firming Cream Sunscreen SPF 10

Crème Rajeunissante et Raffermissante Visage Protection Solaire FPS10

Boots

The Power of Plants

BOTANICS

50ml e 1.69 US Fl. Oz

Face Lift Firming Cream front.jpg

PACKAGE LABEL

ACTIVE INGREDIENTS/ACTIFS: Avobenzone 3.0% Octisalate 2.5% Octinoxate 7.5%

WARNINGS: Avoid getting directly in eyes. If contact occurs rinse thoroughly with cold water. Avoid direct contact with fabric. Colour may vary due to natural extracts.

MISE EN GARDE: Éviter tout contact avec les yeux. En cas de projection, rincer immédiatement à l'eau froide. Éviter tout contact avec du tissu. La couleur peut varier en raison des extraits naturels.

Mfd in the UK for/Fabriqué au R.-U. pour BBI NG2 3AA. UK.

Dist in the USA by/aux É.-U. par Boots Retail USA Inc. Stamford CT 06901.

USA/Canada: Questions? 1-866-75-BOOTS

www.boots.com

Face Lift Firming Cream back.jpg